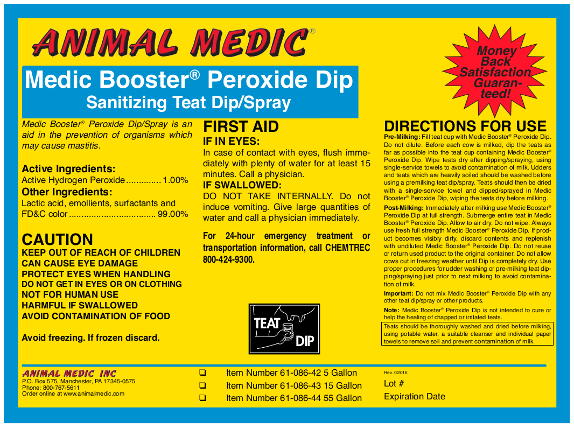 DRUG LABEL: Medic Booster Peroxide Dip
NDC: 12994-002 | Form: LIQUID
Manufacturer: Animal Medic Incorporated
Category: animal | Type: OTC ANIMAL DRUG LABEL
Date: 20160804

ACTIVE INGREDIENTS: HYDROGEN PEROXIDE 10000.0000 mg/1 L

Medic Booster Peroxide Dip

PURPOSE

Sanitizing Teat Dip/Spray

Medic Booster® Peroxide Dip/Spray is an aid in the prevention of organisms which may cause mastitis.

Active Ingredient:

Active Hydrogen Peroxide ......................................... 1.00%

Other Ingredients:

Lactic acid, emollients, surfactants and FD&C color ... 99.00%

USER SAFETY WARNINGS

CAUTION

KEEP OUT OF REACH OF CHILDREN

CAN CAUSE EYE DAMAGE

PROTECT EYES WHEN HANDLING

DO NOT GET IN EYES OR ON CLOTHING

NOT FOR HUMAN USE

HARMFUL IF SWALLOWED

AVOID CONTAMINATION OF FOOD

Avoid freezing.

If frozen, discard.

FIRST AID

IF IN EYES:

In case of contact with eyes, flush immediately with plenty of water for at least 15 minutes.

Call a physician.

IF SWALLOWED:

DO NOT TAKE INTERNALLY.

Do not induce vomiting.

Give large quantities of water and call a physician immediately.

For 24-hour emergency treatment or transportation information, call CHEMTREC 800-424-9300.

DOSAGE AND ADMINISTRATION

DIRECTIONS FOR USE

Pre-Milking: Fill teat cup with Medic Booster® Peroxide Dip. Do not dilute. Before each cow is milked, dip the teats as far as possible into the teat cup containing Medic Booster® Peroxide Dip. Wipe teats dry after dipping/spraying using single-service towels to avoid contamination of milk.

Udders and teats which are heavily soiled should be washed before using a premilking teat dip/spray. Teats should then be dried with a single-service towels and dipped/sprayed in Medic Booster® Peroxide Dip, wiping teats before milking.

Post-Milking: Immediately after milking, use Medic Booster® Peroxide Dip at full strength. Submerge entire teat in Medic Booster® Peroxide Dip. Allow to air dry. Do not wipe.

Always use full strength Medic Booster® Peroxide Dip. If product becomes visibly dirty, discard contents and replenish with undiluted Medic Booster® Peroxide Dip. Do not reuse or return to original container.

Do not allow cows out in freezing weather until dip is completely dry. Use proper procedures for udder washing or pre-milking teat dipping/spraying just prior to next milking to avoid contamination of milk.

Important: Do not mix Medic Booster® Dip with water, any other teat dip/spray or other products

Note: Medic Booster® Peroxide Dip is not intended to cure or help the healing of chapped or irritated teats.

Teats should be thoroughly washed and dried before milking, using potable water, a suitable cleanser and individual paper towels to removed soil and prevent contamination of milk.